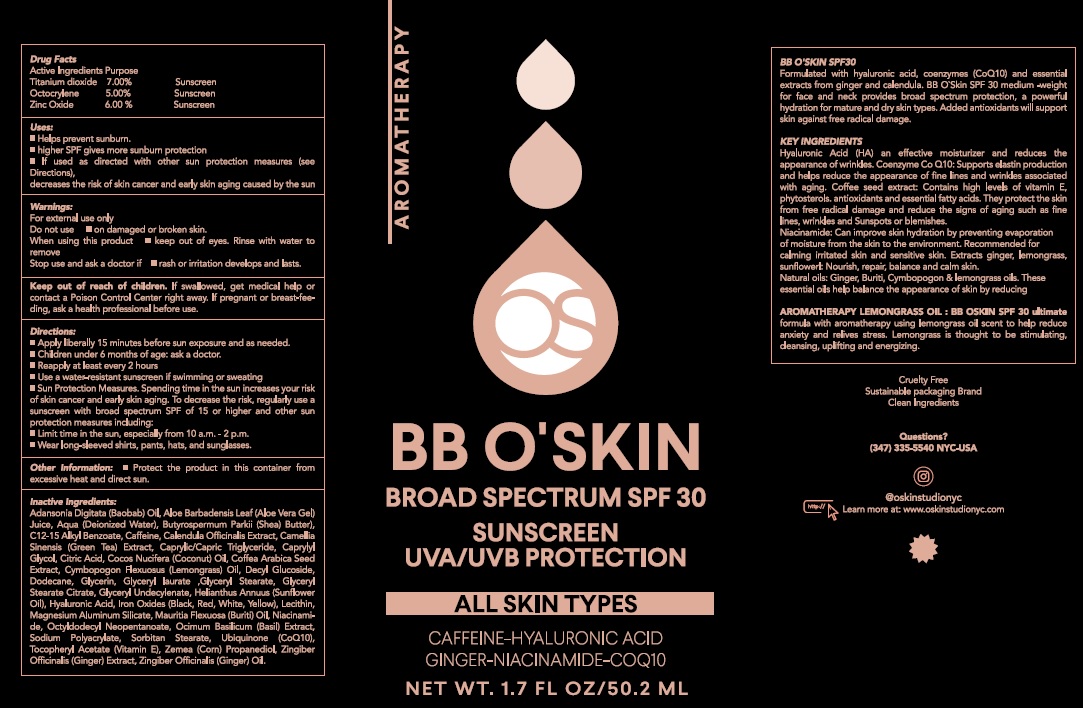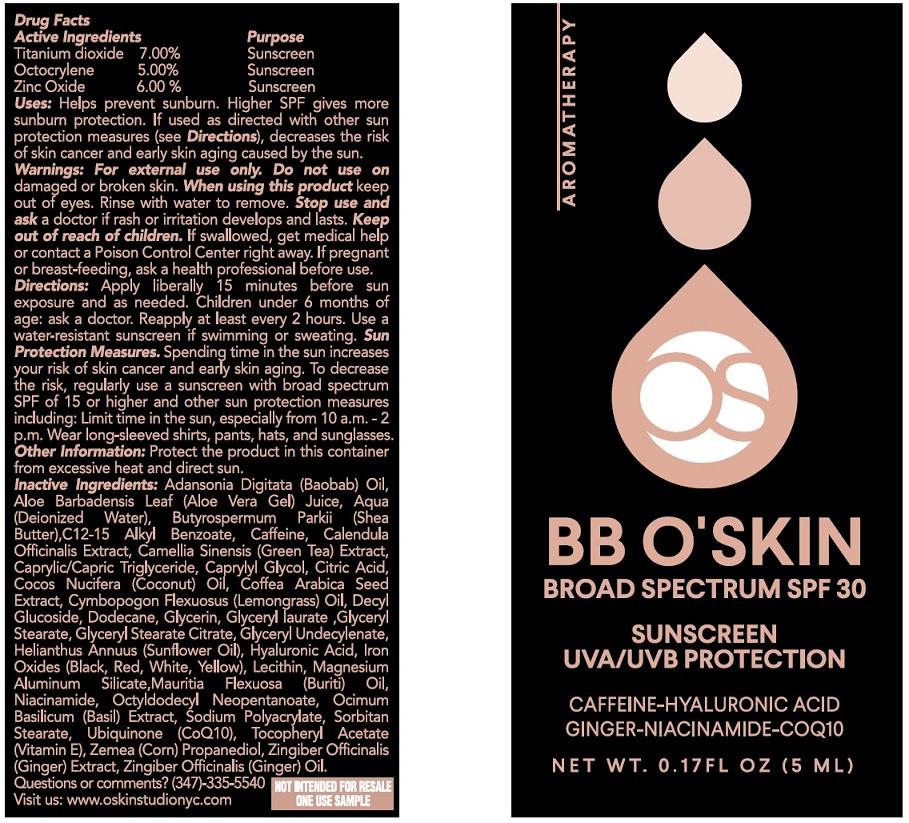 DRUG LABEL: BB OSKIN Broad Spectrum SPF-30
NDC: 83276-390 | Form: CREAM
Manufacturer: O'Skin Studio NY
Category: otc | Type: HUMAN OTC DRUG LABEL
Date: 20231106

ACTIVE INGREDIENTS: TITANIUM DIOXIDE 70 mg/1 mL; OCTOCRYLENE 50 mg/1 mL; ZINC OXIDE 60 mg/1 mL
INACTIVE INGREDIENTS: ADANSONIA DIGITATA SEED OIL; ALOE VERA LEAF; WATER; SHEA BUTTER; ALKYL (C12-15) BENZOATE; CAFFEINE; CALENDULA OFFICINALIS FLOWER; GREEN TEA LEAF; MEDIUM-CHAIN TRIGLYCERIDES; CAPRYLYL GLYCOL; CITRIC ACID MONOHYDRATE; COCONUT OIL; EAST INDIAN LEMONGRASS OIL; DECYL GLUCOSIDE; DODECANE; GLYCERIN; GLYCERYL LAURATE; GLYCERYL MONOSTEARATE; GLYCERYL STEARATE CITRATE; HELIANTHUS ANNUUS FLOWERING TOP; HYALURONIC ACID; FERRIC OXIDE RED; MAGNESIUM ALUMINUM SILICATE; NIACINAMIDE; OCTYLDODECYL NEOPENTANOATE; BASIL; SORBITAN MONOSTEARATE; UBIDECARENONE; .ALPHA.-TOCOPHEROL ACETATE; CORN; GINGER

BB O'SKIN Broad Spectrum SPF-30

Active Ingredients

Titanium dioxide 7.00%

Octocrylene 5.00%

Zinc Oxide 6.00%

Purpose

Sunscreen

Uses:

- Helps prevent sunburn.
- higher SPF gives more sunburn protection
- if used as directed with other sun protection meassures (see Directions), decreases the risk of skin cancer and early skin aging caused by the sun

Warnings:

For external use only

Do not use

- on damaged or broken skin.

When using this product

- keep out of eyes. Rinse with water to remove

Stop use and ask a doctor if

rash or irritation develops and lasts.

Keep out of reach of children.

If swallowed, get medical help or contact a Poison Control Center right away. If pregnant or breast-feeding, ask a health professional before use.

If pregnant or breast-feeding,

ask a health professional before use.

Directions:

- Apply liberally 15 minutes before sun exposure and as needed.
- Children under 6 months of age: ask a doctor.
- Reapply at least every 2 hours
- Use a water-resistant sunscreen if swimming or sweating
- Sun Protection Measures. Spending time in the sun increases your risk of skin cancer and early skin aging. To decrease the risk, regularly use a sunscreen with broad spectrum SPF of 15 or higher and other sun protection measures including:
- Limit time in the sun, expecially from 10 a.m.-2 p.m.
- Wear long-sleevd shirts, pants, hats, and sunglasses.

Other Information:

- Protect the product in this container from excessive heat and direct sun.

Inactive Ingredients:

Adansonia Digitata (Baobab) Oil, Aloe Barbadensis Leaf (Aloe Vera Gel) Juice, Aqua (Deionized Water), Butyrospermum Parkii (Shea Butter), C12-15 Alkyl Benzoate, Caffeine, Calendula Officinalis Extract, Camellia Sinensis (Green Tea) Extract, Caprylic/Capric Triglyceride, Caprylyl Glycol, Citric Acid, Cocos Nucifera (Coconut) Oil, Coffea Arabica Seed Extract, Cymbopogon Flexuosus (Lemongrass) Oil, Decyl Glucoside, Dodecane, Glycerin, Glyceryl laurate, Glyceryl Stearate, Glyceryl Stearate Citrate, Glyceryl Undecylenate, Helianthus Annuus (Sunflower Oil), Hyaluronic Acid, Iron Oxides (Black, Red, White, Yellow), Lecithin, Magnesium Aluminum Silicate, Mauritia Flexuosa (Buriti) Oil, Niacinamide, Octyldodecyl Neopentanoate, Ocimum Basilicum (Basil) Extract, Sodium Polyacrylate, Sorbitan Stearate, Ubiquinone (CoQ10), Tocopheryl Acetate (Vitamin E), Zemea (Corn) Propanediol, Zingiber Officinalis (Ginger) Extract, ZIngiber Officinalis (Ginger) Oil,

Questions or comments?

(347-335-5540) Visit us: www.oskinstudionyc.com